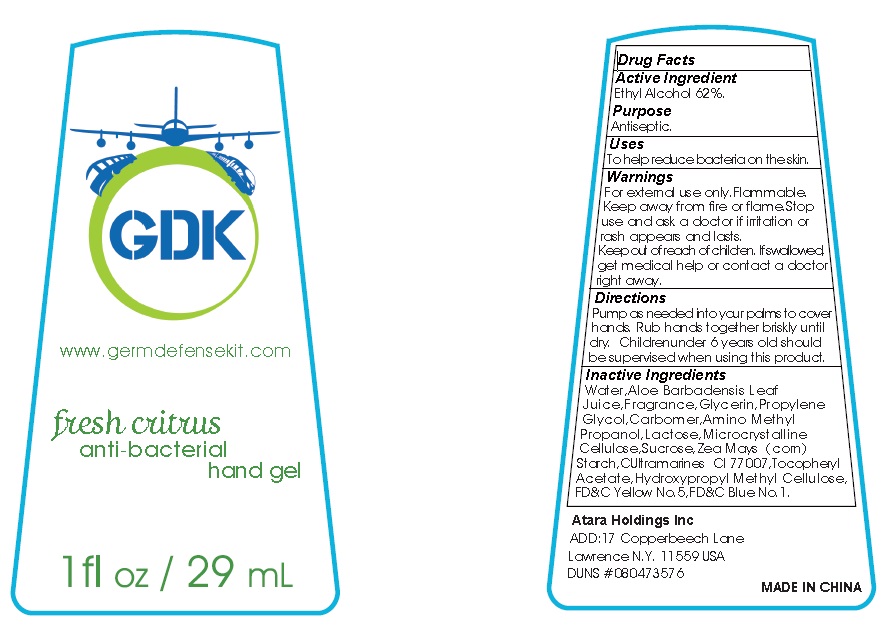 DRUG LABEL: Hand Sanitizer
NDC: 71154-001 | Form: GEL
Manufacturer: Atara Holdings Inc
Category: otc | Type: HUMAN OTC DRUG LABEL
Date: 20161225

ACTIVE INGREDIENTS: ALCOHOL 62 mL/100 mL
INACTIVE INGREDIENTS: WATER; ALOE VERA LEAF; GLYCERIN; PROPYLENE GLYCOL; CARBOMER INTERPOLYMER TYPE A (55000 CPS); AMINOMETHYLPROPANOL; LACTOSE; CELLULOSE, MICROCRYSTALLINE; SUCROSE; STARCH, CORN; ULTRAMARINE BLUE; .ALPHA.-TOCOPHEROL ACETATE; HYPROMELLOSES; FD&C YELLOW NO. 5; FD&C BLUE NO. 1

Active Ingredient
Ethyl Alcohol 62%

Purpose
Antiseptic

Warnings

For external use only. Flammable. Keep away from fire or flame.

Stop use and ask a doctor if irritation or rash appears and lasts.

Keep out of reach of children. If swallowed, get medical help or contact a doctor right away.

Directions

Pump as needed into your palms to cover hands. Rub hands together briskly unitl dry. Children under 6 years old should be supervised when using this product.

Inactive Ingredients

Water, Aloe Barbadensis Leaf Juice, Fragrance, Glycerin, Propylene Glycol, Carbomer, Aminomethyl Propanol, Lactose, Microcrystalline Cellulose, Sucrose, Zea Mays (corn) Starch, Ultramarine Blue CI 77007, Tocopheryl Acetate, Hydroxpropyl Methyl Cellulose, FD&C Yellow No.5, FD&C Blue No.1.

Uses

To help reduce bacteria on the skin.